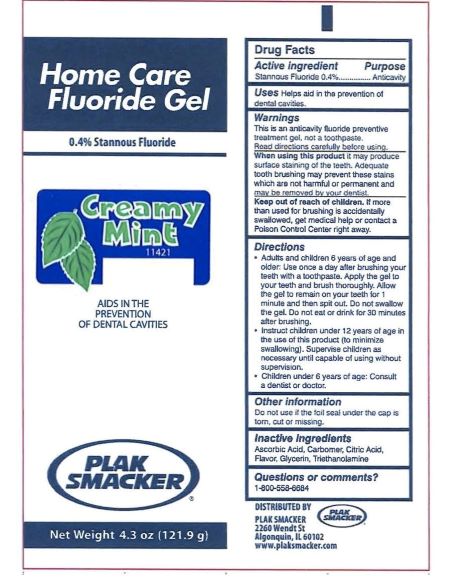 DRUG LABEL: Plak Smacker
NDC: 72796-0411 | Form: GEL
Manufacturer: Young Innovations, Inc.
Category: otc | Type: HUMAN OTC DRUG LABEL
Date: 20251104

ACTIVE INGREDIENTS: STANNOUS FLUORIDE 0.969 mg/1 g
INACTIVE INGREDIENTS: CARBOMER HOMOPOLYMER TYPE B (ALLYL SUCROSE CROSSLINKED); MINT; GLYCERIN; ASCORBIC ACID; ANHYDROUS CITRIC ACID; TROLAMINE

Plak Smacker Stannous Gel - Mint

Active ingredient

Stannous Fluoride 0.4%

Purpose

Anticavity

Uses

Helps aid in the prevention of dental cavities.

Warnings

This is an anticavity fluoride preventive treatment gel, not a toothpaste. Read directions carefully before using.

Warnings

When using this product it may produce surface staining of the teeth. Adequate tooth brushing may prevent these stains which are not harmful or permanent and may be removed by your dentist.

Warnings

Keep out of reach of children. If more than used for brushing is accidentally swallowed, get medical help or contact a Poison Control Center right away.

Directions

- Adults and children 6 years of age and older: Use once a day after brushing your teeth with a toothpaste. Apply the gel to your teeth and brush thoroughly. Allow the gel to remain on your teeth for 1 minute and then spit out. Do not swallow the gel. Do not eat or drink for 30 minutes after brushing.
- Instruct children under 12 years of age in the use of this product (to minimize swallowing). Supervise children as necessary until capable of using without supervision.
- Children under 6 years of age: Consult a dentist or doctor.

Other information

Do not use if the foil seal under the cap is torn, cut of missing.

Inactive ingredients

Ascorbic Acid, Carbomer, Citric Acid, Flavor, Glycerin, Triethanolamine

Questions or comments?

1-800-558-6684

Principal Display Panel

Home Care

Fluoride Gel

0.4% Stannous Fluoride

Creamy

Mint

11421

AIDS IN THE

PREVENTION

OF DENTAL CAVITIES

PLAK

SMACKER

Net Weight 4.3 oz (121.9 g)